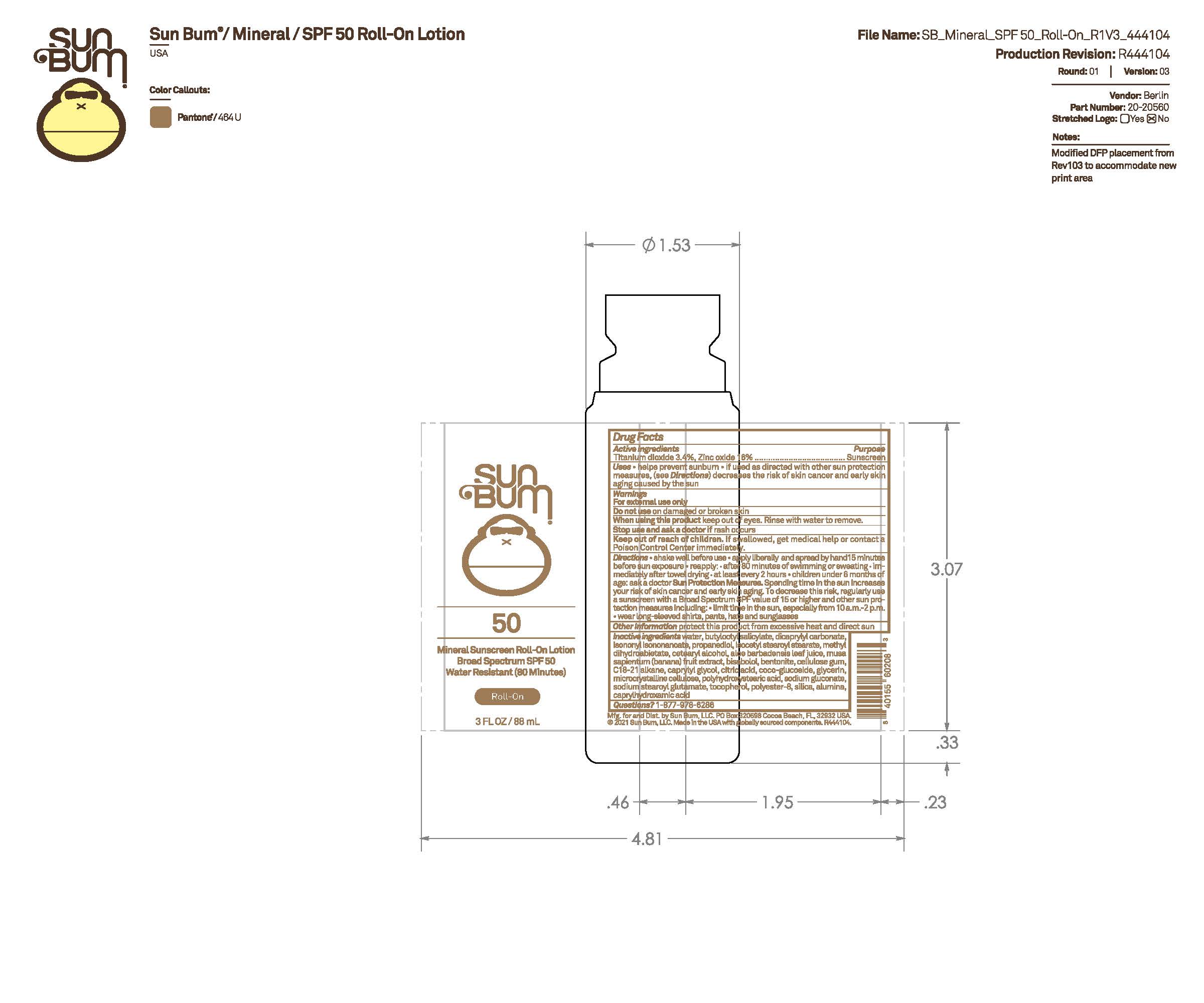 DRUG LABEL: Sun Bum 50 Mineral Sunscreen Roll-On
NDC: 69039-735 | Form: LOTION
Manufacturer: Sun Bum, LLC
Category: otc | Type: HUMAN OTC DRUG LABEL
Date: 20250814

ACTIVE INGREDIENTS: TITANIUM DIOXIDE 34 mg/1 mL; ZINC OXIDE 160 mg/1 mL
INACTIVE INGREDIENTS: BUTYLOCTYL SALICYLATE; ISOCETYL STEAROYL STEARATE; CELLULOSE GUM; DICAPRYLYL CARBONATE; POLYHYDROXYSTEARIC ACID (2300 MW); SODIUM STEAROYL GLUTAMATE; CETEARYL ALCOHOL; BANANA PEEL; COCO-GLUCOSIDE; ALOE BARBADENSIS LEAF JUICE; BENTONITE; GLYCERIN; MICROCRYSTALLINE CELLULOSE; SODIUM GLUCONATE; CAPRYLHYDROXAMIC ACID; METHYL DIHYDROABIETATE; CITRIC ACID; C18-21 ALKANE; ALUMINA; PROPANEDIOL; WATER; BISABOLOL; CAPRYLYL GLYCOL; POLYESTER-8 (1400 MW, CYANODIPHENYLPROPENOYL CAPPED); TOCOPHEROL; SILICA; ISONONYL ISONONANOATE

Sun Bum 50 Mineral Sunscreen Roll-On

Active Ingredients

Titanium Dioxide – 3.4%, Zinc Oxide - 16%

Purpose

Sunscreen

Uses

• helps prevent sunburn • if used as directed with other sun protection measures, (see Directions) decreases the risk of skin cancer and early skin aging caused by the sun

Warnings

For external use only

Do not use on damaged or broken skin

When using this product keep out of eyes. Rinse with water to remove.

Stop use and ask a doctor if rash occurs

Keep out of reach of children. If swallowed, get medical help or contact a Poison Control Center immediately.

Warnings

Keep Out Of Reach Of Children

Directions

• shake well before use

• apply liberally 15 minutes before sun exposure

• reapply: • after 80 minutes of swimming or sweating • immediately after towel drying • at least every 2 hours

• children under 6 months of age: ask a doctor

• Sun Protection Measures. Spending time in the sun increases your risk of skin cancer and early skin aging. To decrease this risk, regularly use a sunscreen with a Broad Spectrum SPF value of 15 or higher and other sun protection measures including:

• limit time in the sun, especially from 10 a.m.- 2 p.m.

• wear long-sleeved shirts, pants, hats and sunglasses

Directions

• shake well before use

• apply liberally 15 minutes before sun exposure

Other Information

protect this product from excessive heat and direct sun

Inactive Ingredients

water, butyloctyl salicylate, dicaprylyl carbonate, isononyl isononanoate, propanediol, isocetyl stearoyl stearate, methyl dihydroabietate, cetearyl alcohol, aloe barbadensis leaf juice, musa sapientum (banana) fruit extract, bisabolol, bentonite, cellulose gum, C18-21 alkane, caprylyl glycol, citric acid, coco-glucoside, glycerin, microcrystalline cellulose, polyhydroxystearic acid, sodium gluconate, sodium stearoyl glutamate, tocopherol, polyester-8, silica, alumina, caprylhydroxamic acid

Questions?

1-877-978-6286